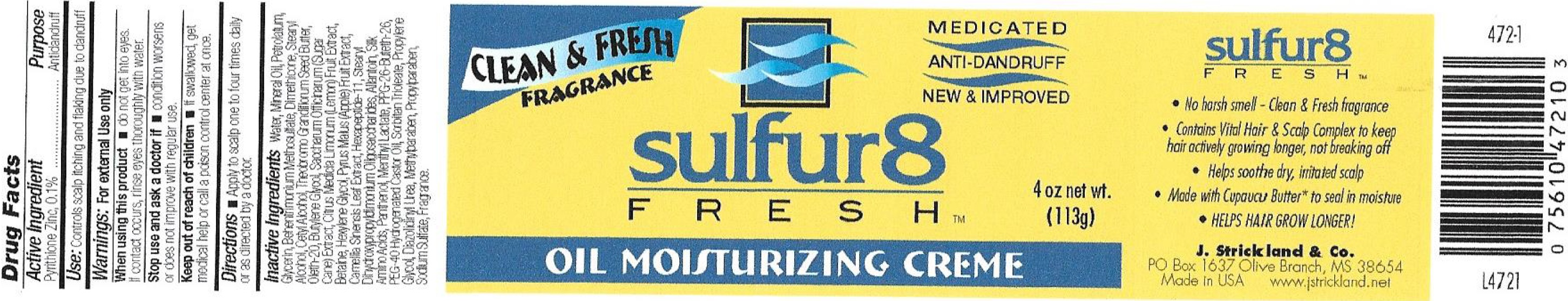 DRUG LABEL: Sulfur 8 Fresh Anti-Dandruff Moisturizing
NDC: 12022-027 | Form: CREAM
Manufacturer: J. Strickland & Co.
Category: otc | Type: HUMAN OTC DRUG LABEL
Date: 20231021

ACTIVE INGREDIENTS: PYRITHIONE ZINC 1 mg/1 g
INACTIVE INGREDIENTS: WATER; MINERAL OIL; PETROLATUM; GLYCERIN; BEHENTRIMONIUM METHOSULFATE; DIMETHICONE; STEARYL ALCOHOL; CETYL ALCOHOL; THEOBROMA GRANDIFLORUM SEED BUTTER; OLETH-20; BUTYLENE GLYCOL; SUGARCANE; BETAINE; HEXYLENE GLYCOL; APPLE; GREEN TEA LEAF; HEXAPEPTIDE-11; ALLANTOIN; AMINO ACIDS, SILK; PANTHENOL; MENTHYL LACTATE, (-)-; PPG-26-BUTETH-26; POLYOXYL 40 HYDROGENATED CASTOR OIL; SORBITAN TRIOLEATE; PROPYLENE GLYCOL; DIAZOLIDINYL UREA; METHYLPARABEN; PROPYLPARABEN; SODIUM SULFATE

Sulfur 8 Fresh Anti-Dandruff Oil Moisturizing Cream

Active Ingredients

Pyrithione Zinc, 0.1%

Purpose

Antidandruff

Use:

Controls scalp itching and flaking due to dandruff

Warnings:

For external use only

When using this product

- do not get into eyes. If contact occurs, rinse eyes thoroughly with water.

Stop use and consult a doctor if

- condition worsens or does not improve after regular use

Keep out of reach of children

If swallowed, get medical help or call a poison control center at once.

Directions

- Apply to the affected area 1-4 times daily, or as directed by a doctor.

Inactive Ingredients

water, Mineral Oil, Aloe Barbadensis Leaf Juice, Isopropyl Myristate, Stearyl Alcohol, Ceteareth-20, Sodium Carbomer, Simmondsia Chinensis (Jojoba) Seed Oil, Hydrolyzed Collagen, Propylene Glycol, Tocopheryl Acetate, Methylparaben, Propylparaben, Diazolidinyl Urea, Sodium Lauryl Sulfate, Panthenol, Fragrance.